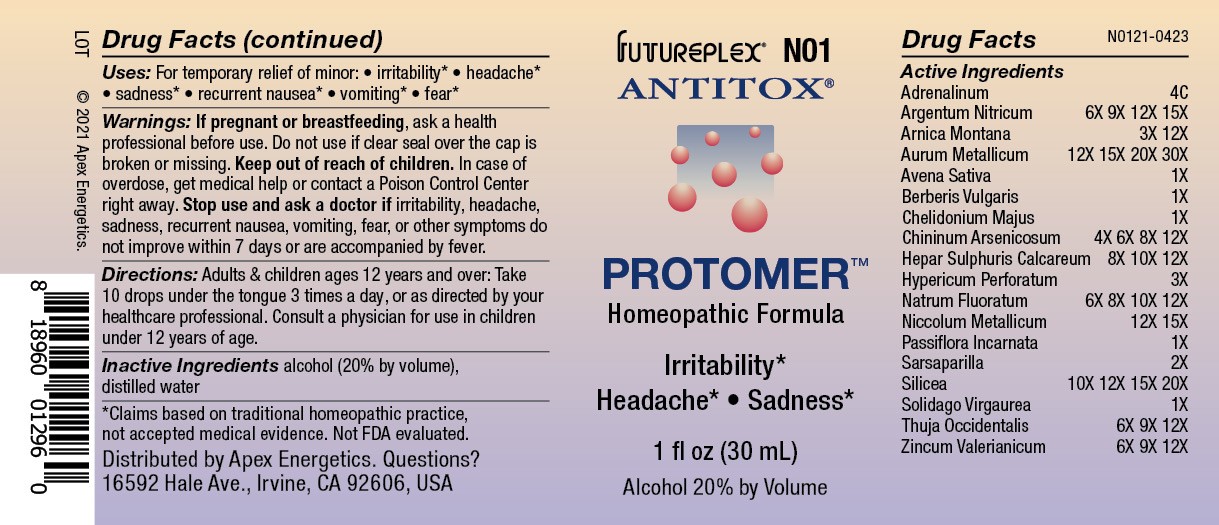 DRUG LABEL: N01
NDC: 63479-1401 | Form: SOLUTION/ DROPS
Manufacturer: Apex Energetics Inc.
Category: homeopathic | Type: HUMAN OTC DRUG LABEL
Date: 20240108

ACTIVE INGREDIENTS: EPINEPHRINE 4 [hp_C]/1 mL; SILVER NITRATE 15 [hp_X]/1 mL; AVENA SATIVA FLOWERING TOP 1 [hp_X]/1 mL; BERBERIS VULGARIS ROOT BARK 1 [hp_X]/1 mL; ARNICA MONTANA 12 [hp_X]/1 mL; SARSAPARILLA 2 [hp_X]/1 mL; GOLD 30 [hp_X]/1 mL; CHELIDONIUM MAJUS 1 [hp_X]/1 mL; NICKEL 15 [hp_X]/1 mL; SILICON DIOXIDE 20 [hp_X]/1 mL; THUJA OCCIDENTALIS LEAFY TWIG 12 [hp_X]/1 mL; SOLIDAGO VIRGAUREA FLOWERING TOP 1 [hp_X]/1 mL; ZINC VALERATE DIHYDRATE 12 [hp_X]/1 mL; CALCIUM SULFIDE 12 [hp_X]/1 mL; SODIUM FLUORIDE 12 [hp_X]/1 mL; QUININE ARSENITE 12 [hp_X]/1 mL; HYPERICUM PERFORATUM 3 [hp_X]/1 mL; PASSIFLORA INCARNATA TOP 1 [hp_X]/1 mL
INACTIVE INGREDIENTS: ALCOHOL; WATER

N01

Active Ingredients
Adrenalinum | 4C
Argentum Nitricum | 6X 9X 12X 15X
Arnica Montana | 3X 12X
Aurum Metallicum | 12X 15X 20X 30X
Avena Sativa | 1X
Berberis Vulgaris | 1X
Chelidonium Majus | 1X
Chininum Arsenicosum | 4X 6X 8X 12X
Hepar Sulphuris Calcareum | 8X 10X 12X
Hypericum Perforatum | 3X
Natrum Fluoratum | 6X 8X 10X 12X
Niccolum Metallicum | 12X 15X
Passiflora Incarnata | 1X
Sarsaparilla | 2X
Silicea | 10X 12X 15X 20X
Solidago Virgaurea | 1X
Thuja Occidentalis | 6X 9X 12X
Zincum Valerianicum | 6X 9X 12X

INDICATIONS AND USAGE

Uses:

For temporary relief of minor:

irritability*

headache*

sadness*

recurrent nausea*

vomiting*

fear*

*Claims based on traditional homeopathic practice, not accepted medical evidence. Not FDA evaluated.

Warnings:

PREGNANCY OR BREAST FEEDING

If pregnant or breastfeeding, ask a health professional before use.

Do not use if clear seal over the cap is broken or missing.

Keep out of reach of children. In case of overdose, get medical help or contact a Poison Control Center right away.

Stop use and ask a doctor if irritability, headache, sadness, recurrent nausea, vomiting, fear, or other symptoms do not improve within 7 days or are accompanied by fever.

Directions:

Adults & children ages 12 years and over: Take 10 drops under the tongue 3 times a day, or as directed by your healthcare professional. Consult a physician for use in children under 12 years of age.

Inactive Ingredients

alcohol (20% by volume), distilled water

Distributed by Apex Energetics. Questions?

16592 Hale Ave., Irvine, CA 92606, USA

PACKAGE LABEL

FUTUREPLEX® N01

ANTITOX®

PROTOMER™

Homeopathic Formula

Irritability*

Headache* Sadness*

1 fl oz (30 mL)

Alcohol 20% by Volume